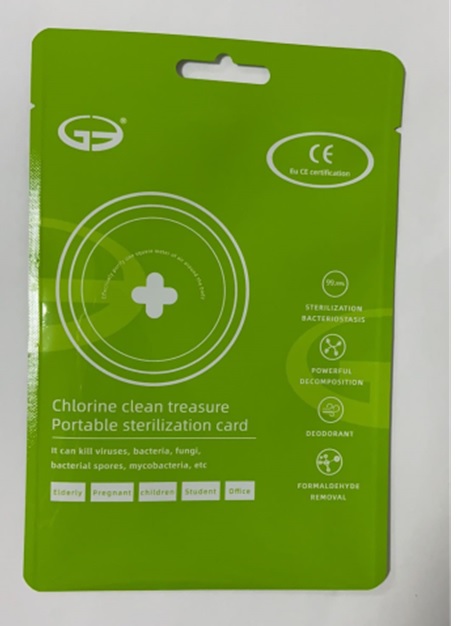 DRUG LABEL: CLO2--Portable sterilization card
NDC: 77261-201 | Form: POWDER
Manufacturer: Shenzhen Haiyin Hongye Technology Co., Ltd.
Category: otc | Type: HUMAN OTC DRUG LABEL
Date: 20200509

ACTIVE INGREDIENTS: CHLORIC ACID 10 g/15 g
INACTIVE INGREDIENTS: CGP-68730A FREE ACID; BETADEX; MAGNESIUM SULFATE HEPTAHYDRATE; GOLOTIMOD; CALCIUM SULFATE

Portable sterilization card

CLO2--Portable sterilization card

Active Ingredient(s)

Chlorine dioxide 10g/15g. Purpose: Antiseptic

Purpose

Antiseptic, Portable sterilization card

Use

Portable sterilization card to help reduce bacteria that potentially can cause disease.

Warnings

For external use only. Flammable. Keep away from heat or flame

Do not use

- in children less than 2 months of age
- on open skin wounds

When using this product keep out of eyes, ears, and mouth. In case of contact with eyes, rinse eyes thoroughly with water.
Stop use and ask a doctor if irritation or rash occurs. These may be signs of a serious condition.
Keep out of reach of children. If swallowed, get medical help or contact a Poison Control Center right away.

Stop use and ask a doctor if irritation or rash occurs. These may be signs of a serious condition.

Keep out of reach of children. If swallowed, get medical help or contact a Poison Control Center right away.

Directions

- Take it with you, the gas it releases can kill bacteria
- Supervise children under 6 years of age when using this product to avoid swallowing.

Other information

- Store between 15-30C (59-86F)
- Avoid freezing and excessive heat above 40C (104F)

Inactive ingredients

Urea nitrate
Magnesium sulfate
Calcium sulphate
Superabsorbent acrylic resin
Beta cyclodextrins